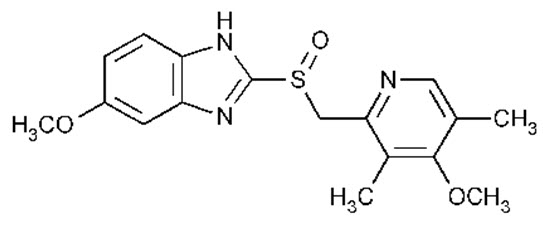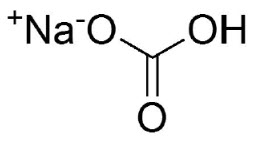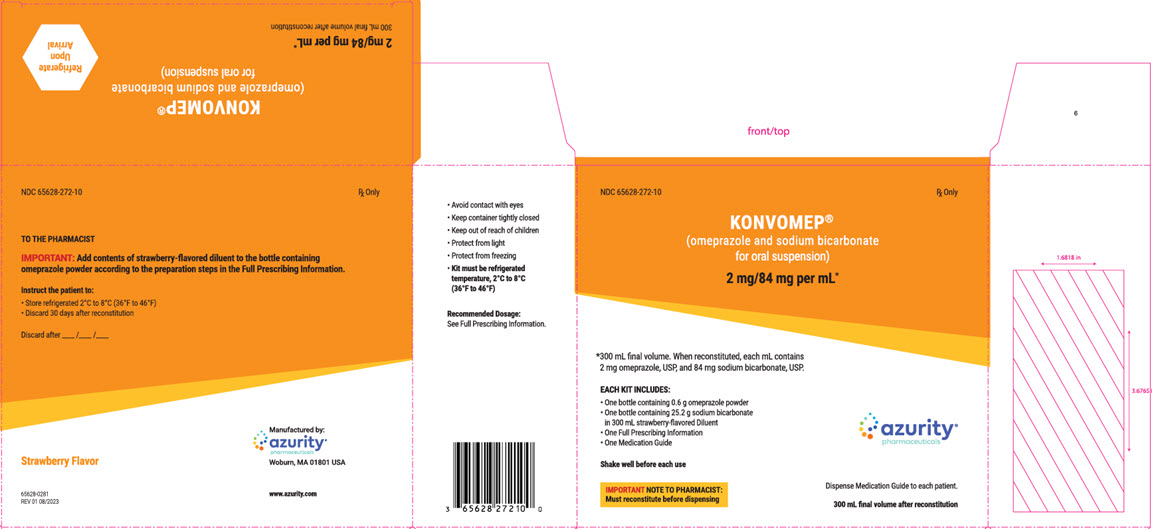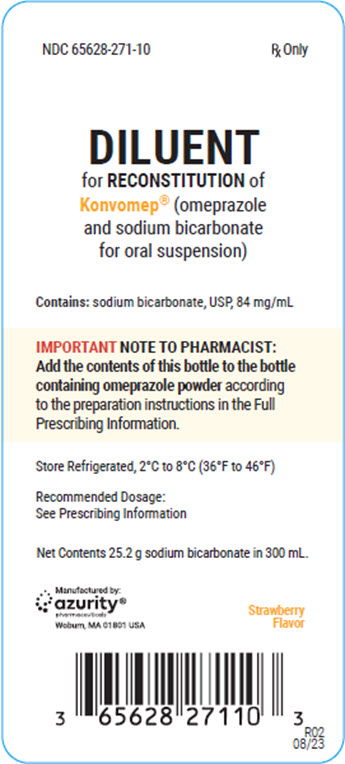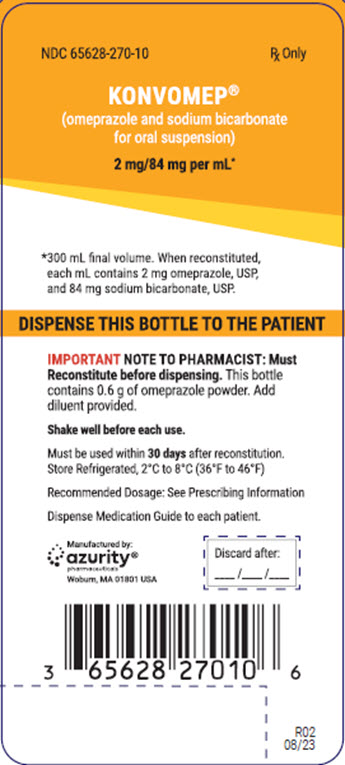 DRUG LABEL: Konvomep
NDC: 65628-272 | Form: KIT | Route: ORAL
Manufacturer: Azurity Pharmaceuticals, Inc.
Category: prescription | Type: HUMAN PRESCRIPTION DRUG LABEL
Date: 20251216

ACTIVE INGREDIENTS: OMEPRAZOLE 2 mg/1 mL; SODIUM BICARBONATE 84 mg/1 mL; OMEPRAZOLE 2 mg/1 mL; SODIUM BICARBONATE 84 mg/1 mL; OMEPRAZOLE 2 mg/1 mL; SODIUM BICARBONATE 84 mg/1 mL
INACTIVE INGREDIENTS: BENZYL ALCOHOL; CARBOXYMETHYLCELLULOSE SODIUM, UNSPECIFIED FORM; FD&C RED NO. 40; POLOXAMER 188; WATER; DIMETHICONE; SILICON DIOXIDE; TRISODIUM CITRATE DIHYDRATE; SORBITOL SOLUTION; PROPYLENE GLYCOL; GLYCERIN; SUCRALOSE; BENZYL ALCOHOL; CARBOXYMETHYLCELLULOSE SODIUM, UNSPECIFIED FORM; FD&C RED NO. 40; POLOXAMER 188; WATER; DIMETHICONE; SILICON DIOXIDE; TRISODIUM CITRATE DIHYDRATE; SORBITOL SOLUTION; PROPYLENE GLYCOL; GLYCERIN; SUCRALOSE; BENZYL ALCOHOL; CARBOXYMETHYLCELLULOSE SODIUM, UNSPECIFIED FORM; FD&C RED NO. 40; POLOXAMER 188; WATER; DIMETHICONE; SILICON DIOXIDE; TRISODIUM CITRATE DIHYDRATE; SORBITOL SOLUTION; PROPYLENE GLYCOL; GLYCERIN; SUCRALOSE

HIGHLIGHTS OF PRESCRIBING INFORMATION

These highlights do not include all the information needed to use KONVOMEPsafely and effectively. See full prescribing information for KONVOMEP.
KONVOMEP®(omeprazole and sodium bicarbonate for oral suspension)
Initial U.S. Approval: 2004

1 INDICATIONS AND USAGE

KONVOMEP is a combination of omeprazole, a proton pump inhibitor (PPI) and sodium bicarbonate, indicated in adults for:

•Treatment of active benign gastric ulcer (1)

•Reduction of risk of upper gastrointestinal (GI) bleeding in critically ill patients (1)

2 DOSAGE AND ADMINISTRATION

Recommended doses of KONVOMEP in the table below are based upon the omeprazole content. (2.2)

Indication | Recommended Adult Dosage (2.2)
Active Benign Gastric Ulcer | 40 mg once daily for 4 to 8 weeks
Reduction of Risk of Upper GI Bleeding in Critically Ill Patients | 40 mg initially followed by 40 mg 6 to 8 hours later and 40 mg once daily thereafter for 14 days

3 DOSAGE FORMS AND STRENGTHS

For Oral Suspension: 2 mg omeprazole and 84 mg sodium bicarbonate per mL after reconstitution in 90 mL, 150 mL, or 300 mL bottles. (3)

4 CONTRAINDICATIONS

- Known hypersensitivity to any components of the formulation (4)
- Patients receiving rilpivirine‑containing products (4, 7)

5 WARNINGS AND PRECAUTIONS

- Gastric Malignancy: In adults, symptomatic response does not preclude the presence of gastric malignancy. Consider additional follow-up and diagnostic testing. (5.1)
- Acute Tubulointerstitial Nephritis: Discontinue treatment and evaluate patients. (5.2)
- Sodium Content: Take sodium content into consideration in patients on a sodium-restricted diet. Avoid in patients with Bartter’s syndrome, hypokalemia, hypocalcemia, and problems with acid-base balance. (5.3)
- Clostridium difficile-Associated Diarrhea : PPI therapy may be associated with increased risk. (5.4)
- Bone Fracture: Long-term and multiple daily dose PPI therapy may be associated with an increased risk for osteoporosis-related fractures of the hip, wrist, or spine. (5.5)
- Severe Cutaneous Adverse Reactions: Discontinue at the first signs or symptoms of severe cutaneous adverse reactions or other signs of hypersensitivity and consider further evaluation. (5.6)
- Cutaneous and Systemic Lupus Erythematosus: Mostly cutaneous; new onset or exacerbation of existing disease; discontinue KONVOMEP and refer to specialist for evaluation. (5.7)
- Interaction with Clopidogrel: Avoid concomitant use of KONVOMEP. (5.8)
- Cyanocobalamin (Vitamin B-12) Deficiency: Daily long-term use (e.g., longer than 3 years) may lead to malabsorption or a deficiency of cyanocobalamin. (5.9)
- Hypomagnesemia and Mineral Metabolism: Reported rarely with prolonged treatment with PPIs. (5.10)
- Interaction with St. John’s Wort or Rifampin: Avoid concomitant use of KONVOMEP. (5.11, 7)
- Interactions with Diagnostic Investigations for Neuroendocrine Tumors: Increased Chromogranin A (CgA) levels may interfere with diagnostic investigations for neuroendocrine tumors; temporarily stop KONVOMEP at least 14 days before assessing CgA levels. (5.12)
- Interaction with Methotrexate: Concomitant use with PPIs may elevate and/or prolong serum concentrations of methotrexate and/or its metabolite, possibly leading to toxicity. With high dose methotrexate administration, consider a temporary withdrawal of KONVOMEP. (5.13, 7)
- Fundic Gland Polyps: Risk increases with long-term use, especially beyond one year. Use the shortest duration of therapy. (5.14)

6 ADVERSE REACTIONS

Most common adverse reactions (≥2%) are: headache, abdominal pain, nausea, diarrhea, vomiting, and flatulence. (6.1)

To report SUSPECTED ADVERSE REACTIONS, contact Azurity Pharmaceuticals, Inc. at 1-800-461-7449 or FDA at 1-800-FDA-1088 or www.fda.gov/medwatch.

7 DRUG INTERACTIONS

See Full Prescribing Information for a list of clinically important drug interactions. (7)

FULL PRESCRIBING INFORMATION

1 INDICATIONS AND USAGE

KONVOMEP is indicated in adults for:

- short-term treatment (4 to 8 weeks) of active benign gastric ulcer.
- reduction of risk of upper gastrointestinal (GI) bleeding in critically ill adult patients.

2 DOSAGE AND ADMINISTRATION

2.1 Important Administration Instructions

•KONVOMEP is a kit of two bottles: one bottle containing omeprazole powder and one bottle of diluent containing sodium bicarbonate.

•KONVOMEP is for reconstitution by a healthcare provider for use in adults.

•After reconstitution, each mL of KONVOMEP contains 2 mg of omeprazole and 84 mg of sodium bicarbonate.

•Take the sodium content of KONVOMEP into consideration when prescribing this product [see Warnings and Precautions (5.3)] .

•Recommended doses throughout the labeling are based upon the omeprazole component of KONVOMEP.

2.2 Dosage Regimen

The recommended dosage regimen in adults of KONVOMEP by indication is summarized in Table 1. Recommended dosage is based upon the omeprazole content of KONVOMEP.

Table 1: Recommended Dosage Regimen of KONVOMEP for Adults by Indication
Indication | Recommended Dosage | Treatment Duration
Treatment of Benign Gastric Ulcer | 40 mg once daily | 4 to 8 weeks
Reduction of Risk of Upper GI Bleeding in Critically Ill Patients | 40 mg initially; followed by 40 mg 6 to 8 hours later; and 40 mg once daily thereafter | 14 days

2.3 Preparation and Administration

Preparation of Reconstituted Suspension by a Healthcare Provider Prior to Dispensing

1.Hold the neck of the bottle containing the omeprazole powder and tap all four of the bottom edges on a hard surface to loosen the powder.2.Shake the diluent containing sodium bicarbonate for a few seconds. Open the diluent bottle and transfer about one-third of the contents into the bottle containing omeprazole powder, replace the omeprazole powder cap, and shake the bottle vertically for approximately 30 seconds.3.Add a second one-third of the diluent into the omeprazole powder bottle and shake the bottle vigorously for approximately 30 seconds.4.Add the remaining diluent into the omeprazole powder bottle. Allow diluent to drain into the omeprazole powder bottle for 10 seconds and shake the omeprazole bottle vigorously for approximately 30 seconds.5.The reconstituted suspension contains 40 mg of omeprazole per 20 mL and should be pink to red and hazy.6.Instruct the patient to shake the reconstituted suspension well before each use. Use an oral dosing device that measures the appropriate volume.

Nasogastric or Orogastric Tube Administration (8 French or larger)

If KONVOMEP is administered via nasogastric or orogastric tube, suspend enteral feeding approximately 3 hours before and 1 hour after administration of KONVOMEP.

1.Reconstitute KONVOMEP according to the steps for preparation provided above.2.Use a catheter or oral tip syringe to administer KONVOMEP through the nasogastric or orogastric tube.3.Shake the bottle well prior to dispensing 20 mL of KONVOMEP into the syringe.4.Immediately inject the medication through the nasogastric or orogastric tube into the stomach.5.Refill the syringe with 20 mL of water.6.Flush any remaining medication from the nasogastric or orogastric tube into the stomach.

Storage of Reconstituted Suspension

Store the reconstituted KONVOMEP suspension under refrigerated conditions 2°C to 8°C (36°F to 46°F) for up to 30 days.

3 DOSAGE FORMS AND STRENGTHS

For Oral Suspension: 2 mg omeprazole and 84 mg sodium bicarbonate per mL of a pink to red hazy, strawberry-flavored liquid after reconstitution in 90 mL, 150 mL, or 300 mL bottles. Each kit contains a bottle of omeprazole as a white to off-white powder and a strawberry-flavored diluent containing sodium bicarbonate as a slightly hazy red liquid [see Description (11) and How Supplied/Storage and Handling (16)] .

4 CONTRAINDICATIONS

KONVOMEP is contraindicated in patients with known hypersensitivity to substituted benzimidazoles or to any components of the formulation. Hypersensitivity reactions may include anaphylaxis, anaphylactic shock, angioedema, bronchospasm, acute tubulointerstitial nephritis, and urticaria [see Warnings and Precautions (5.2) and Adverse Reactions (6.2)] .

Proton pump inhibitors (PPIs), including KONVOMEP, are contraindicated in patients receiving rilpivirine containing products [see Drug Interactions (7)] .

5 WARNINGS AND PRECAUTIONS

5.1 Presence of Gastric Malignancy

In adults, symptomatic response to therapy with KONVOMEP does not preclude the presence of gastric malignancy. Consider additional follow-up and diagnostic testing in adult patients who have a suboptimal response or an early symptomatic relapse after completing treatment with a proton pump inhibitor (PPI). In older patients, also consider an endoscopy.

5.2 Acute Tubulointerstitial Nephritis

Acute tubulointerstitial nephritis (TIN) has been observed in patients taking PPIs and may occur at any point during PPI therapy. Patients may present with varying signs and symptoms from symptomatic hypersensitivity reactions to non-specific symptoms of decreased renal function (e.g., malaise, nausea, anorexia). In reported case series, some patients were diagnosed on biopsy and in the absence of extra-renal manifestations (e.g., fever, rash or arthralgia).

Discontinue KONVOMEP and evaluate patients with suspected acute TIN [see Contraindications (4)] .

5.3 Sodium Content

Each mL of reconstituted KONVOMEP contains 84 mg of sodium bicarbonate (equivalent to 1 mEq/mL of sodium). The total content of sodium, from active and inactive ingredients per mL of reconstituted KONVOMEP is 26.3 mg (1.14 mEq). Total sodium content per 40 mg dose (volume of 20 mL) of KONVOMEP is 526 mg (22.8 mEq).

Chronic administration of bicarbonate with calcium or milk can cause milk-alkali syndrome. Chronic use of sodium bicarbonate may lead to systemic alkalosis, and increased sodium intake can produce edema and weight gain.

The sodium content of KONVOMEP should be taken into consideration when administering to patients on a sodium-restricted diet or those at risk for developing congestive heart failure.

Avoid KONVOMEP in patients with Bartter’s syndrome, hypokalemia, hypocalcemia, and problems with acid‑base balance.

5.4 Clostridium difficile-Associated Diarrhea

Published observational studies suggest that PPI therapy like KONVOMEP may be associated with an increased risk of Clostridium difficile-associated diarrhea, especially in hospitalized patients. This diagnosis should be considered for diarrhea that does not improve [see Adverse Reactions (6.2)] .

Patients should use the lowest dose and shortest duration of PPI therapy appropriate to the condition being treated.

5.5 Bone Fracture

Several published observational studies suggest that PPI therapy may be associated with an increased risk for osteoporosis-related fractures of the hip, wrist, or spine. The risk of fracture was increased in patients who received high-dose, defined as multiple daily doses, and long-term PPI therapy (a year or longer). Patients should use the lowest dose and shortest duration of PPI therapy appropriate to the condition being treated. Patients at risk for osteoporosis-related fractures should be managed according to the established treatment guidelines [see Dosage and Administration (2.2) and Adverse Reactions (6.2)] .

5.6 Severe Cutaneous Adverse Reactions

Severe cutaneous adverse reactions, including Stevens-Johnson syndrome (SJS) and toxic epidermal necrolysis (TEN), drug reaction with eosinophilia and systemic symptoms (DRESS), and acute generalized exanthematous pustulosis (AGEP) have been reported in association with the use of PPIs [see Adverse Reactions (6.2)] . Discontinue KONVOMEP at the first signs or symptoms of severe cutaneous adverse reactions or other signs of hypersensitivity and consider further evaluation.

5.7 Cutaneous and Systemic Lupus Erythematosus

Cutaneous lupus erythematosus (CLE) and systemic lupus erythematosus (SLE) have been reported in patients taking PPIs, including omeprazole. These events have occurred as both new onset and an exacerbation of existing autoimmune disease. The majority of PPI-induced lupus erythematous cases were CLE.

The most common form of CLE reported in patients treated with PPIs was subacute CLE (SCLE) and occurred within weeks to years after continuous drug therapy in patients ranging from infants to the elderly. Generally, histological findings were observed without organ involvement.

Systemic lupus erythematosus (SLE) is less commonly reported than CLE in patients receiving PPIs. PPI associated SLE is usually milder than non-drug induced SLE. Onset of SLE typically occurred within days to years after initiating treatment in patients ranging from young adults to the elderly. The majority of patients presented with rash; however, arthralgia and cytopenia were also reported.

Avoid administration of PPIs for longer than medically indicated. If signs or symptoms consistent with CLE or SLE are noted in patients receiving KONVOMEP, discontinue the drug and refer the patient to the appropriate specialist for evaluation. Most patients improve with discontinuation of the PPI alone in 4 to 12 weeks. Serological testing (e.g., ANA) may be positive and elevated serological test results may take longer to resolve than clinical manifestations.

5.8 Interaction with Clopidogrel

Avoid concomitant use of KONVOMEP with clopidogrel. Clopidogrel is a prodrug. Inhibition of platelet aggregation by clopidogrel is entirely due to an active metabolite. The metabolism of clopidogrel to its active metabolite can be impaired by use with concomitant medications, such as omeprazole, that interfere with CYP2C19 activity. Concomitant use of clopidogrel with 80 mg omeprazole reduces the pharmacological activity of clopidogrel, even when administered 12 hours apart. When using KONVOMEP, consider alternative antiplatelet therapy [see Drug Interactions (7) and Clinical Pharmacology (12.3)] .

5.9 Cyanocobalamin (Vitamin B-12) Deficiency

Daily treatment with any acid-suppressing medications over a long period of time (e.g., longer than 3 years) may lead to malabsorption of cyanocobalamin (vitamin B-12) caused by hypo or achlorhydria. Rare reports of cyanocobalamin deficiency occurring with acid-suppressing therapy have been reported in the literature. This diagnosis should be considered if clinical symptoms consistent with cyanocobalamin deficiency are observed in patients treated with KONVOMEP.

5.10 Hypomagnesemia and Mineral Metabolism

Hypomagnesemia, symptomatic and asymptomatic, has been reported rarely in patients treated with PPIs for at least three months, in most cases after a year of therapy. Serious adverse events include tetany, arrhythmias, and seizures.

Hypomagnesemia may lead to hypocalcemia and/or hypokalemia and may exacerbate underlying hypocalcemia in at-risk patients. In most patients, treatment of hypomagnesemia required magnesium replacement and discontinuation of the PPI.

For patients expected to be on prolonged treatment or who take PPIs with medications such as digoxin or drugs that may cause hypomagnesemia (e.g., diuretics), health care professionals may consider monitoring magnesium levels prior to initiation of PPI treatment and periodically [see Adverse Reactions (6.2)] .

Consider monitoring magnesium and calcium levels prior to initiation of KONVOMEP and periodically while on treatment in patients with a preexisting risk of hypocalcemia (e.g., hypoparathyroidism). Supplement with magnesium and/or calcium as necessary. If hypocalcemia is refractory to treatment, consider discontinuing the PPI.

5.11 Interaction with St. John’s Wort or Rifampin

Drugs which induce CYP2C19 or CYP3A4 (such as St. John’s wort or rifampin) can substantially decrease omeprazole concentrations [see Drug Interactions (7)] . Avoid concomitant use of KONVOMEP with St. John’s wort or rifampin.

5.12 Interactions with Investigations for Neuroendocrine Tumors

Serum chromogranin A (CgA) levels increase secondary to drug-induced decreases in gastric acidity. The increased CgA level may cause false positive results in diagnostic investigations for neuroendocrine tumors. Providers should temporarily stop KONVOMEP treatment for at least 14 days before assessing CgA levels and consider repeating the test if initial CgA levels are high. If serial tests are performed (e.g., for monitoring), the same commercial laboratory should be used for testing, as reference ranges between tests may vary [see Drug Interactions (7)] .

5.13 Interaction with Methotrexate

Literature suggests that concomitant use of PPIs with methotrexate (primarily at high-dose) may elevate and prolong serum levels of methotrexate and/or its metabolite, possibly leading to methotrexate toxicities. In high‑dose methotrexate administration, a temporary withdrawal of the PPI may be considered in some patients [see Drug Interactions (7)] .

5.14 Fundic Gland Polyps

PPI use is associated with an increased risk of fundic gland polyps that increases with long-term use, especially beyond one year. Most PPI users who developed fundic gland polyps were asymptomatic and fundic gland polyps were identified incidentally on endoscopy. Use the shortest duration of PPI therapy appropriate to the condition being treated.

6 ADVERSE REACTIONS

The following serious adverse reactions are described below and elsewhere in labeling:

- Acute Tubulointerstitial Nephritis [see Warnings and Precautions (5.2)] .
- Clostridium difficile-Associated Diarrhea [see Warnings and Precautions (5.4)] .
- Bone Fracture [see Warnings and Precautions (5.5)] .
- Severe Cutaneous Adverse Reactions [see Warnings and Precautions (5.6)] .
- Cutaneous and Systemic Lupus Erythematosus [see Warnings and Precautions (5.7)] .
- Cyanocobalamin (Vitamin B-12) Deficiency [see Warnings and Precautions (5.9)] .
- Hypomagnesemia and Mineral Metabolism [see Warnings and Precautions (5.10)] .
- Fundic Gland Polyps [see Warnings and Precautions (5.14)] .

6.1 Clinical Trials Experience

Because clinical trials are conducted under widely varying conditions, adverse reaction rates observed in the clinical trials of a drug cannot be directly compared to rates in the clinical trials of another drug and may not reflect the rates observed in practice.

The safety of KONVOMEP has been established, in part, based on oral studies of an oral delayed-release omeprazole product and another oral omeprazole and sodium bicarbonate product.

Clinical Trials with Omeprazole

In the U.S. clinical trial population of 465 adult patients, the adverse reactions summarized in Table 2were reported to occur in 1% or more of patients on therapy with omeprazole.

Table 2: Adverse Reactions Occurring in 1% or More of Adult Patients in US Clinical Trials of Omeprazole Therapy
 | Omeprazole % (n = 465) | Placebo % (n = 64) | Ranitidine % (n = 195)
Headache | 7 | 6 | 8
Diarrhea | 3 | 3 | 2
Abdominal Pain | 2 | 3 | 3
Nausea | 2 | 3 | 4
Upper Respiratory Infection (URI) | 2 | 2 | 3
Dizziness | 2 | 0 | 3
Vomiting | 2 | 5 | 2
Rash | 2 | 0 | 0
Constipation | 1 | 0 | 0
Cough | 1 | 0 | 2
Asthenia | 1 | 2 | 2
Back Pain | 1 | 0 | 1

Table 3summarizes the adverse reactions that occurred in 1% or more of omeprazole-treated patients from international double-blind and open-label clinical trials in which 2631 patients and subjects received omeprazole.

Table 3: Adverse Reactions Occurring in 1% or More of Adult Patients in International Clinical Trials of Omeprazole Therapy
 | Omeprazole % (n = 2631) | Placebo % (n = 120)
Abdominal Pain | 5.2 | 3.3
Nausea | 4.0 | 6.7
Diarrhea | 3.7 | 2.5
Vomiting | 3.2 | 10.0
Headache | 2.9 | 2.5
Flatulence | 2.7 | 5.8
Acid Regurgitation | 1.9 | 3.3
Constipation | 1.5 | 0.8
Asthenia | 1.3 | 0.8

Clinical Trial of Another Omeprazole and Sodium Bicarbonate Product, 40 mg

Adverse reactions reported in at least 3% of critically ill adult patients in a clinical trial of 40 mg omeprazole and sodium bicarbonate for oral suspension compared to intravenous cimetidine for up to 14 days are presented in Table 4.

Table 4: Common Adverse Reactions [Reported in at least 3% of patients in either treatment group.] by Body System and Preferred Term in a Randomized Controlled Trial of Critically Ill Adult Patients Treated up to 14 Days
Body System Preferred Term | Omeprazole and Sodium Bicarbonate for Oral Suspension, 40 mg (%) (n = 178) | Intravenous Cimetidine 1,200 mg per day (%) (n = 181)
Blood and Lymphatic System Disorders
Anemia NOS | 7.9 | 7.7
Anemia NOS Aggravated | 2.2 | 3.9
Thrombocytopenia | 10.1 | 6.1
Cardiac Disorders
Atrial Fibrillation | 6.2 | 3.9
Bradycardia NOS | 3.9 | 2.8
Supraventricular Tachycardia | 3.4 | 1.1
Tachycardia NOS | 3.4 | 3.3
Ventricular Tachycardia | 4.5 | 3.3
Gastrointestinal Disorders [In this trial, clinically significant upper gastrointestinal bleeding was considered a serious adverse reaction, but it is not included in this table.]
Constipation | 4.5 | 4.4
Diarrhea NOS | 3.9 | 8.3
Gastric Hypomotility | 1.7 | 3.3
General Disorders and Administration Site Conditions
Hyperpyrexia | 4.5 | 1.7
Edema NOS | 2.8 | 6.1
Pyrexia | 20.2 | 16.0
Infections and Infestations
Candidal Infection NOS | 1.7 | 3.9
Oral Candidiasis | 3.9 | 0.6
Sepsis NOS | 5.1 | 5.0
Urinary Tract Infection | 2.2 | 3.3
Investigations
Liver Function Tests NOS Abnormal | 1.7 | 3.3
Metabolism and Nutrition Disorders
Fluid Overload | 5.1 | 7.7
Hyperglycemia NOS | 10.7 | 11.6
Hyperkalemia | 2.2 | 3.3
Hypernatremia | 1.7 | 5.0
Hypocalcemia | 6.2 | 5.5
Hypoglycemia NOS | 3.4 | 4.4
Hypokalemia | 12.4 | 13.3
Hypomagnesemia | 10.1 | 9.9
Hyponatremia | 3.9 | 2.8
Hypophosphatemia | 6.2 | 3.9
Psychiatric Disorders
Agitation | 3.4 | 8.8
Respiratory, Thoracic, and Mediastinal Disorders
Acute Respiratory Distress Syndrome | 3.4 | 3.9
Nosocomial Pneumonia | 11.2 | 9.4
Pneumothorax NOS | 0.6 | 4.4
Respiratory Failure | 1.7 | 3.3
Skin and Subcutaneous Tissue Disorders
Decubitus Ulcer | 3.4 | 2.8
Rash NOS | 5.6 | 6.1
Vascular Disorders
Hypertension NOS | 7.9 | 3.3
Hypotension NOS | 9.6 | 6.6
NOS = Not otherwise specified.

6.2 Postmarketing Experience

The following adverse reactions have been identified during post-approval use of omeprazole and sodium bicarbonate. Because these reactions are reported voluntarily from a population of uncertain size, it is not always possible to reliably estimate their frequency or establish a causal relationship to drug exposure.

Omeprazole

Body as a Whole:Hypersensitivity reactions, including anaphylaxis, anaphylactic shock, angioedema, bronchospasm, urticaria (see also Skinbelow), fever, pain, fatigue, malaise, and systemic lupus erythematosus.

Cardiovascular:Chest pain or angina, tachycardia, bradycardia, palpitation, elevated blood pressure, and peripheral edema.

Gastrointestinal:Pancreatitis (some fatal), anorexia, irritable colon, flatulence, fecal discoloration, esophageal candidiasis, mucosal atrophy of the tongue, dry mouth, stomatitis, abdominal swelling and fundic gland polyps. Gastroduodenal carcinoids have been reported in patients with Zollinger-Ellison syndrome on long-term treatment with omeprazole. This finding is believed to be a manifestation of the underlying condition, which is known to be associated with such tumors.

Hepatic:Mild and, rarely, marked elevations of liver function tests [ALT (SGPT), AST (SGOT), ᵞ-glutamyl transpeptidase, alkaline phosphatase, and bilirubin (jaundice)]. In rare instances, overt liver disease has occurred, including hepatocellular, cholestatic, or mixed hepatitis, liver necrosis (some fatal), hepatic failure (some fatal), and hepatic encephalopathy.

Infections and Infestations: Clostridium difficile-associated diarrhea.

Metabolism and Nutritional Disorders:Hypomagnesemia, hypocalcemia, hypokalemia, [see Warnings and Precautions (5.10)] , hyponatremia, hypoglycemia and weight gain.

Musculoskeletal:Muscle cramps, myalgia, muscle weakness, joint pain, bone fracture, and leg pain.

Nervous System/Psychiatric:Psychic disturbances including depression, agitation, aggression, hallucinations, confusion, insomnia, nervousness, tremors, apathy, somnolence, anxiety, dream abnormalities; vertigo; paresthesia; and hemifacial dysesthesia.

Respiratory:Epistaxis, pharyngeal pain.

Skin:Severe generalized skin reactions including TEN (some fatal), SJS, DRESS, AGEP, cutaneous lupus erythematosus and erythema multiforme (some severe); purpura and/or petechiae (some with rechallenge); skin inflammation, urticaria, angioedema, pruritus, photosensitivity, alopecia, dry skin, and hyperhidrosis.

Special Senses:Tinnitus, taste perversion.

Ocular:Blurred vision, ocular irritation, dry eye syndrome, optic atrophy, anterior ischemic optic neuropathy, optic neuritis, and double vision.

Urogenital:Tubulointerstitial nephritis, urinary tract infection, microscopic pyuria, urinary frequency, elevated serum creatinine, proteinuria, hematuria, glycosuria, testicular pain, gynecomastia, and erectile dysfunction.

Hematologic:Rare instances of pancytopenia, agranulocytosis (some fatal), thrombocytopenia, neutropenia, leukopenia, anemia, leukocytosis, and hemolytic anemia have been reported.

Sodium Bicarbonate

Metabolic alkalosis, seizures, and tetany.

7 DRUG INTERACTIONS

Table 5and Table 6include drugs with clinically important drug interactions and interaction with diagnostics when administered concomitantly with omeprazole and instructions for preventing or managing them.

Consult the labeling of concomitantly used drugs to obtain further information about interactions with PPIs.

Table 5: Clinically Relevant Interactions Affecting Drugs Co-Administered with Omeprazole and Interaction with Diagnostics
Antiretrovirals
Clinical Impact: | The effect of PPIs on antiretroviral drugs is variable. The clinical importance and the mechanisms behind these interactions are not always known.; - Decreased exposure of some antiretroviral drugs (e.g., rilpivirine, atazanavir and nelfinavir) when used concomitantly with omeprazole may reduce antiviral effect and promote the development of drug resistance [see Clinical Pharmacology (12.3)] . - Increased exposure of other antiretroviral drugs (e.g., saquinavir) when used concomitantly with omeprazole may increase toxicity [see Clinical Pharmacology (12.3)] . - There are other antiretroviral drugs which do not result in clinically relevant interactions with omeprazole.
Intervention: | Rilpivirine-containing products: Concomitant use with KONVOMEP is contraindicated [see Contraindications (4)] .; Atazanavir: Avoid concomitant use with KONVOMEP. See prescribing information for atazanavir for dosing information.; Nelfinavir: Avoid concomitant use with KONVOMEP. See prescribing information for nelfinavir.; Saquinavir: See the prescribing information for saquinavir for monitoring of potential saquinavir-related toxicities.; Other antiretrovirals: See prescribing information for specific antiretroviral drugs.
Warfarin
Clinical Impact: | Increased INR and prothrombin time in patients receiving PPIs, including omeprazole, and warfarin concomitantly. Increases in INR and prothrombin time may lead to abnormal bleeding and even death.
Intervention: | Monitor INR and prothrombin time and adjust the dose of warfarin, if needed, to maintain target INR range.
Methotrexate
Clinical Impact: | Concomitant use of omeprazole with methotrexate (primarily at high dose) may elevate and prolong serum concentrations of methotrexate and/or its metabolite hydroxymethotrexate, possibly leading to methotrexate toxicities. No formal drug interaction studies of high-dose methotrexate with PPIs have been conducted [see Warnings and Precautions (5.13)] .
Intervention: | A temporary withdrawal of KONVOMEP may be considered in some patients receiving high‑dose methotrexate.
CYP2C19 Substrates (e.g., clopidogrel, citalopram, cilostazol, phenytoin, diazepam)
Clopidogrel
Clinical Impact: | Concomitant use of omeprazole 80 mg results in reduced plasma concentrations of the active metabolite of clopidogrel and a reduction in platelet inhibition [see Clinical Pharmacology (12.3)] .
Clinical Impact: | There are no adequate combination studies of a lower dose of omeprazole or a higher dose of clopidogrel in comparison with the approved dose of clopidogrel.
Intervention: | Avoid concomitant use with KONVOMEP. Consider use of alternative anti-platelet therapy [see Warnings and Precautions (5.8)] .
Citalopram
Clinical Impact: | Increased exposure of citalopram leading to an increased risk of QT prolongation [see Clinical Pharmacology (12.3)] .
Intervention: | Limit the dose of citalopram to a maximum of 20 mg per day. See prescribing information for citalopram.
Cilostazol
Clinical Impact: | Increased exposure of one of the active metabolites of cilostazol (3,4-dihydro-cilostazol) [see Clinical Pharmacology (12.3)] .
Intervention: | Reduce the dose of cilostazol to 50 mg twice daily. See prescribing information for cilostazol.
Phenytoin
Clinical Impact: | Potential for increased exposure of phenytoin.
Intervention: | Monitor phenytoin serum concentrations. Dose adjustment may be needed to maintain therapeutic drug concentrations. See prescribing information for phenytoin.
Diazepam
Clinical Impact: | Increased exposure of diazepam [see Clinical Pharmacology (12.3)] .
Intervention: | Monitor patients for increased sedation and reduce the dose of diazepam as needed.
Digoxin
Clinical Impact: | Potential for increased exposure of digoxin [see Clinical Pharmacology (12.3)] .
Intervention: | Monitor digoxin concentrations. Dose adjustment may be needed to maintain therapeutic drug concentrations. See digoxin prescribing information.
Drugs Dependent on Gastric pH for Absorption (e.g., iron salts, erlotinib, dasatinib, nilotinib, mycophenolate mofetil, ketoconazole/itraconazole)
Clinical Impact: | Omeprazole can reduce the absorption of other drugs due to its effect on reducing intragastric acidity.
Intervention: | Mycophenolate mofetil (MMF): Co-administration of omeprazole in healthy subjects and in transplant patients receiving MMF has been reported to reduce the exposure to the active metabolite, mycophenolic acid (MPA), possibly due to a decrease in MMF solubility at an increased gastric pH. The clinical relevance of reduced MPA exposure on organ rejection has not been established in transplant patients receiving KONVOMEP and MMF. Use KONVOMEP with caution in transplant patients receiving MMF [see Clinical Pharmacology (12.3)] .; See the prescribing information for other drugs dependent on gastric pH for absorption.
Tacrolimus
Clinical Impact: | Potential for increased exposure of tacrolimus, especially in transplant patients who are intermediate or poor metabolizers of CYP2C19.
Intervention: | Monitor tacrolimus whole blood concentrations. Dose adjustment may be needed to maintain therapeutic drug concentrations. See prescribing information for tacrolimus.
Interactions with Investigations of Neuroendocrine Tumors
Clinical Impact: | Serum chromogranin A (CgA) levels increase secondary to PPI-induced decreases in gastric acidity. The increased CgA level may cause false positive results in diagnostic investigations for neuroendocrine tumors [see Warnings and Precautions (5.12) and Clinical Pharmacology (12.2)] .
Intervention: | Temporarily stop KONVOMEP treatment at least 14 days before assessing CgA levels and consider repeating the test if initial CgA levels are high. If serial tests are performed (e.g., for monitoring), the same commercial laboratory should be used for testing, as reference ranges between tests may vary.
Interaction with Secretin Stimulation Test
Clinical Impact: | Hyper-response in gastrin secretion in response to secretin stimulation test, falsely suggesting gastrinoma.
Intervention: | Temporarily stop KONVOMEP treatment at least 14 days before assessing to allow gastrin levels to return to baseline [see Clinical Pharmacology (12.2)] .
False Positive Urine Tests for THC
Clinical Impact: | There have been reports of false positive urine screening tests for tetrahydrocannabinol (THC) in patients receiving PPIs.
Intervention: | An alternative confirmatory method should be considered to verify positive results.
Other
Clinical Impact: | There have been clinical reports of interactions with other drugs metabolized via the cytochrome P450 system (e.g., cyclosporine, disulfiram).
Intervention: | Monitor patients to determine if it is necessary to adjust the dosage of these other drugs when taken concomitantly with KONVOMEP.

Table 6: Clinically Relevant Interactions Affecting Omeprazole when Co-Administered with Other Drugs
CYP2C19 or CYP3A4 Inducers
Clinical Impact: | Decreased exposure of omeprazole when used concomitantly with strong inducers [see Clinical Pharmacology (12.3)] .
Intervention: | St. John’s Wort, rifampin: Avoid concomitant use with KONVOMEP [see Warnings and Precautions (5.11)] .; Ritonavir-containing products: see prescribing information for specific drugs.
CYP2C19 or CYP3A4 Inhibitors
Clinical Impact: | Increased exposure of omeprazole [see Clinical Pharmacology (12.3)] .
Intervention: | Voriconazole: Dosage adjustment of KONVOMEP is not usually required. See full prescribing information for voriconazole.

8 USE IN SPECIFIC POPULATIONS

8.1 Pregnancy

Risk Summary

There are no adequate and well-controlled studies with KONVOMEP in pregnant women. KONVOMEP contains omeprazole and sodium bicarbonate.

Omeprazole

There are no adequate and well-controlled studies with omeprazole in pregnant women. Available epidemiologic data fail to demonstrate an increased risk of major congenital malformations or other adverse pregnancy outcomes with first trimester omeprazole use (see Data). Reproduction studies in rats and rabbits resulted in dose-dependent embryo-lethality at omeprazole doses that were approximately 3.4 to 34 times an oral human dose of 40-mg (based on a body surface area for a 60‑kg person).

Teratogenicity was not observed in animal reproduction studies with administration of oral esomeprazole (an enantiomer of omeprazole) magnesium in rats and rabbits during organogenesis with doses about 68‑times and 42‑times, respectively, an oral human dose of 40‑mg esomeprazole or 40 mg omeprazole (based on body surface area for a 60‑kg person). Changes in bone morphology were observed in offspring of rats dosed through most of pregnancy and lactation at doses equal to or greater than approximately 34-times an oral human dose of 40‑mg esomeprazole or 40‑mg omeprazole. When maternal administration was confined to gestation only, there were no effects on bone physeal morphology in the offspring at any age (see Data).

Sodium Bicarbonate

Available data with sodium bicarbonate use in pregnant women have not identified a drug associated risk of major birth defects or miscarriage. Published animal studies report that sodium bicarbonate administered to rats, mice or rabbits during pregnancy did not cause adverse developmental effects in offspring.

The estimated background risks of major birth defects and miscarriage for the indicated population are unknown. All pregnancies have a background risk of birth defect, loss or other adverse outcomes. In the U.S. general population, the estimated background risk of major birth defects and miscarriage in clinically recognized pregnancies is 2% to 4% and 15% to 20%, respectively.

Data

Human Data

There are no adequate and well-controlled studies with KONVOMEP in pregnant women. Four published epidemiological studies compared the frequency of congenital abnormalities among infants born to women who used omeprazole during pregnancy with the frequency of abnormalities among infants of women exposed to H2‑receptor antagonists or other controls.

A population-based retrospective cohort epidemiological study from the Swedish Medical Birth Register, covering approximately 99% of pregnancies, from 1995 to 99, reported on 955 infants (824 exposed during the first trimester with 39 of these exposed beyond first trimester, and 131 exposed after the first trimester) whose mothers used omeprazole during pregnancy. The number of infants exposed in‑uteroto omeprazole that had any malformation, low birth weight, low Apgar score or hospitalization was similar to the number observed in this population. The number of infants born with ventricular septal defects and the number of stillborn infants was slightly higher in the omeprazole‑exposed infants than the expected number in this population.

A population-based retrospective cohort study covering all live births in Denmark from 1996 to 2009 reported on 1,800 live births whose mothers used omeprazole during the first trimester of pregnancy and 837,317 live births whose mothers did not use any PPI. The overall rate of birth defects in infants born to mothers with first trimester exposure to omeprazole was 2.9% and 2.6% in infants born to mothers not exposed to any PPI during the first trimester.

A retrospective cohort study reported on 689 pregnant women exposed to either H2‑blockers or omeprazole in the first trimester (134 exposed to omeprazole) and 1,572 pregnant women unexposed to either during the first trimester. The overall malformation rate in offspring born to mothers with first trimester exposure to omeprazole, an H2‑blocker, or were unexposed was 3.6%, 5.5%, and 4.1%, respectively.

A small prospective observational cohort study followed 113 women exposed to omeprazole during pregnancy (89% first trimester exposures). The reported rate of major congenital malformations was 4% in the omeprazole group, 2% in controls exposed to non-teratogens, and 2.8% in disease-paired controls. Rates of spontaneous and elective abortions, preterm deliveries, gestational age at delivery, and mean birth weight were similar among the groups.

Several studies have reported no apparent adverse short-term effects on the infant when single-dose oral or intravenous omeprazole was administered to over 200 pregnant women as premedication for cesarean section under general anesthesia.

Animal Data

Omeprazole

Reproductive studies conducted with omeprazole in rats at oral doses up to 138 mg/kg/day (about 34 times an oral human dose of 40 mg on a body surface area basis) and in rabbits at doses up to 69.1 mg/kg/day (about 34 times an oral human dose of 40 mg on a body surface area basis) during organogenesis did not disclose any evidence for a teratogenic potential of omeprazole. In rabbits, omeprazole in a dose range of 6.9 to 69.1 mg/kg/day (about 3.4 to 34 times an oral human dose of 40 mg on a body surface area basis) administered during organogenesis produced dose-related increases in embryo-lethality, fetal resorptions, and pregnancy disruptions. In rats, dose-related embryo/fetal toxicity and postnatal developmental toxicity were observed in offspring resulting from parents treated with omeprazole at 13.8 to 138.0 mg/kg/day (about 3.4 to 34 times an oral human dose of 40 mg on a body surface area basis), administered prior to mating through the lactation period.

Esomeprazole

The data described below was generated from studies using esomeprazole, an enantiomer of omeprazole. The animal to human dose multiples are based on the assumption of equal systemic exposure to esomeprazole in humans following oral administration of either 40 mg esomeprazole or 40 mg omeprazole.

No effects on embryo-fetal development were observed in reproduction studies with esomeprazole magnesium in rats at oral doses up to 280 mg/kg/day (about 68 times an oral human dose of 40 mg on a body surface area basis) and in rabbits at oral doses up to 86 mg/kg/day (about 42 times an oral human dose of 40 mg of esomeprazole or 40 mg omeprazole on a body surface area basis) administered during organogenesis.

A pre- and postnatal developmental toxicity study in rats with additional endpoints to evaluate bone development were performed with esomeprazole magnesium at oral doses of 14 to 280 mg/kg/day (about 3.4 to 68 times an oral human dose of 40 mg of esomeprazole or 40 mg omeprazole on a body surface area basis). Neonatal/early postnatal (birth to weaning) survival was decreased at doses equal to or greater than 138 mg/kg/day (about 34 times an oral human dose of 40 mg esomeprazole or 40 mg omeprazole on a body surface area basis). Body weight and body weight gain were reduced and neurobehavioral or general developmental delays in the immediate post-weaning timeframe were evident at doses equal to or greater than 69 mg/kg/day (about 17 times an oral human dose of 40 mg esomeprazole or 40 mg omeprazole on a body surface area basis). In addition, decreased femur length, width and thickness of cortical bone, decreased thickness of the tibial growth plate and minimal to mild bone marrow hypocellularity were noted at doses of esomeprazole magnesium equal to or greater than 14 mg/kg/day (about 3.4 times an oral human dose of 40 mg esomeprazole or 40 mg omeprazole on a body surface area basis). Physeal dysplasia in the femur was observed in offspring of rats treated with oral doses of esomeprazole magnesium at doses equal to or greater than 138 mg/kg/day (about 34 times an oral human dose of 40 mg esomeprazole or 40 mg omeprazole on a body surface area basis).

Effects on maternal bone were observed in pregnant and lactating rats in a pre- and postnatal toxicity study when esomeprazole magnesium was administered at oral doses of 14 to 280 mg/kg/day (about 3.4 to 68 times an oral human dose of 40 mg esomeprazole or 40 mg omeprazole on a body surface area basis). When rats were dosed from gestational Day 7 through weaning on postnatal Day 21, a statistically significant decrease in maternal femur weight of up to 14% (as compared to placebo treatment) was observed at doses of esomeprazole magnesium equal to or greater than 138 mg/kg/day (about 34 times an oral human dose of 40 mg on a body surface area basis).

A pre- and postnatal development study in rats with esomeprazole strontium (using equimolar doses compared to esomeprazole magnesium study) produced similar results in dams and pups as described above.

A follow up developmental toxicity study in rats with further time points to evaluate pup bone development from postnatal Day 2 to adulthood was performed with esomeprazole magnesium at oral doses of 280 mg/kg/day (about 68 times an oral human dose of 40 mg on a body surface area basis) where esomeprazole administration was from either gestational Day 7 or gestational Day 16 until parturition. When maternal administration was confined to gestation only, there were no effects on bone physeal morphology in the offspring at any age.

8.2 Lactation

Risk Summary

Available data from the published literature suggest both components of KONVOMEP, omeprazole and sodium bicarbonate, are present in human milk. There are no clinical data on the effects of omeprazole or sodium bicarbonate on the breastfed infant or on milk production. The developmental and health benefits of breastfeeding should be considered along with the mother's clinical need for KONVOMEP and any potential adverse effects on the breastfed infant from KONVOMEP or from the underlying maternal condition.

8.4 Pediatric Use

Safety and effectiveness of KONVOMEP have not been established in pediatric patients.

Juvenile Animal Data

Esomeprazole, an enantiomer of omeprazole, was shown to decrease body weight, body weight gain, femur weight, femur length, and overall growth at oral doses about 34 to 68 times a daily human dose of 40 mg esomeprazole or 40 mg omeprazole based on body surface area in a juvenile rat toxicity study. The animal to human dose multiples are based on the assumption of equal systemic exposure to esomeprazole in humans following oral administration of either 40 mg esomeprazole or 40 mg omeprazole.

A 28-day toxicity study with a 14-day recovery phase was conducted in juvenile rats with esomeprazole magnesium at doses of 70 to 280 mg/kg/day (about 17 to 68 times a daily oral human dose of 40 mg esomeprazole or 40 mg omeprazole on a body surface area basis). An increase in the number of deaths at the high dose of 280 mg/kg/day was observed when juvenile rats were administered esomeprazole magnesium from postnatal Day 7 through postnatal Day 35. In addition, doses equal to or greater than 140 mg/kg/day (about 34 times a daily oral human dose of 40 mg esomeprazole or 40 mg omeprazole on a body surface area basis), produced treatment-related decreases in body weight (approximately 14%) and body weight gain, decreases in femur weight and femur length, and affected overall growth. Comparable findings described above have also been observed in this study with another esomeprazole salt, esomeprazole strontium, at equimolar doses of esomeprazole.

8.5 Geriatric Use

Omeprazole was administered to over 2000 elderly individuals (65 years of age or older) in clinical trials in the U.S. and Europe. There were no differences in safety and effectiveness between the elderly and younger subjects. Other reported clinical experience has not identified differences in response between the elderly and younger subjects, but greater sensitivity of some older individuals cannot be ruled out.

Pharmacokinetic studies with buffered omeprazole have shown the elimination rate was somewhat decreased in the elderly and bioavailability was increased. The plasma clearance of omeprazole was 250 mL/min (about half that of young subjects). The plasma half-life averaged one hour, about twice that in nonelderly, healthy subjects taking omeprazole. However, no dosage adjustment is necessary in the elderly [see Clinical Pharmacology (12.3)] .

10 OVERDOSAGE

If over-exposure occurs, call your Poison Control Center at 1-800-222-1222 for current information on the management of poisoning or overdosage.

Omeprazole

Reports have been received of overdosage with omeprazole in humans. Doses ranged up to 2400 mg (120 times the usual recommended clinical dose). Manifestations were variable, but included confusion, drowsiness, blurred vision, tachycardia, nausea, vomiting, diaphoresis, flushing, headache, dry mouth and other adverse reactions similar to those seen in normal clinical experience with the recommended dosage [see Adverse Reactions (6)] . Symptoms were transient, and no serious clinical outcome has been reported when omeprazole was taken alone. No specific antidote for omeprazole overdosage is known. Omeprazole is extensively protein bound and is, therefore, not readily dialyzable. In the event of overdosage, treatment should be symptomatic and supportive.

Sodium Bicarbonate

Overdosage of sodium bicarbonate can cause electrolyte abnormalities (hypocalcemia, hypokalemia, hypernatremia), metabolic alkalosis and seizures. Institute supportive care and correct electrolyte abnormalities.

11 DESCRIPTION

KONVOMEP (omeprazole and sodium bicarbonate for oral suspension) is a combination of omeprazole, a PPI, and sodium bicarbonate, an antacid. Omeprazole is a substituted benzimidazole, 5-methoxy-2-[[(4-methoxy-3,5-dimethyl-2-pyridinyl)methyl]sulfinyl]-1 H-benzimidazole, a racemic mixture of two enantiomers that inhibits gastric acid secretion. Its empirical formula is C17H19N3O3S, with a molecular weight of 345.42. The structural formula is:

Omeprazole is a white to off-white crystalline powder which melts with decomposition at about 155°C. It is a weak base, freely soluble in ethanol and methanol, slightly soluble in acetone and isopropanol and very slightly soluble in water. The stability of omeprazole is a function of pH; it is rapidly degraded in acid media but has acceptable stability under alkaline conditions. Sodium bicarbonate raises the gastric pH and protects the omeprazole from acid degradation.

Sodium bicarbonate is a white crystalline powder. It is soluble in water and insoluble in alcohol. One gram of sodium bicarbonate dissolves in 12 mL of water at 25ºC. The pH of a freshly prepared 0.1 molar aqueous solution is 8.3 at 25ºC. Aqueous solutions slowly convert to sodium carbonate through loss of carbon dioxide.

The molecular formula is NaHCO3and the molecular weight is 84.01. The structural formula is:

KONVOMEP is supplied as a kit. Each kit is comprised of 1 bottle of pre‑weighed omeprazole powder and 1 bottle of pre‑measured strawberry‑flavored diluent to be reconstituted for oral administration. The strawberry‑flavored diluent contains sodium bicarbonate and the following inactive ingredients: benzyl alcohol, carboxymethylcellulose sodium, FD&C Red No. 40, poloxamer 188, purified water, simethicone emulsion, sodium citrate (dihydrate), sorbitol solution, strawberry flavor (natural and artificial flavors, propylene glycol, and glycerin), and sucralose. After reconstitution each mL contains 2 mg omeprazole and 84 mg sodium bicarbonate.

12 CLINICAL PHARMACOLOGY

12.1 Mechanism of Action

Omeprazole belongs to a class of antisecretory compounds, the substituted benzimidazoles, that suppress gastric acid secretion by specific inhibition of the H+/K+ ATPase enzyme system at the secretory surface of the gastric parietal cell. Because this enzyme system is regarded as the acid (proton) pump within the gastric mucosa, omeprazole has been characterized as a gastric acid-pump inhibitor, in that it blocks the final step of acid production. This effect is dose related and leads to inhibition of both basal and stimulated acid secretion irrespective of the stimulus.

12.2 Pharmacodynamics

Antisecretory Activity

Results from a pharmacokinetic/pharmacodynamic (PK/PD) study of the antisecretory effect of repeated once‑daily dosing of 40 mg omeprazole and 1,680 mg sodium bicarbonate for oral suspension in healthy subjects are shown in
Table 7.

Table 7: Effect of Omeprazole and Sodium Bicarbonate on Intragastric pH, Day 7
Parameter | Once Daily Dosage of Omeprazole and Sodium Bicarbonate
Parameter | 40 mg Omeprazole and 1680 mg Sodium Bicarbonate (n = 24)
% Decrease from Baseline for Integrated Gastric Acidity (mmol•hr/L) | 84%
Coefficient of Variation | 20%
% Time Gastric pH > 4 (Hours) | 77% (18.6 hours)
Coefficient of Variation | 27%
Median pH | 5.2
Coefficient of Variation | 17%
Note: Values represent medians. All parameters were measured over a 24-hour period.

The antisecretory effect lasts longer than would be expected from the very short (1 hour) plasma half-life, apparently due to irreversible binding to the parietal H+/K+ ATPase enzyme.

Enterochromaffin-like (ECL) Cell Effects

Human gastric biopsy specimens have been obtained from more than 3000 patients treated with omeprazole in long-term clinical trials. The incidence of ECL cell hyperplasia in these studies increased with time; however, no case of ECL cell carcinoids, dysplasia, or neoplasia has been found in these patients. These studies are of insufficient duration and size to rule out the possible influence of long-term administration of omeprazole on the development of any premalignant or malignant conditions.

Serum Gastrin Effects

In studies involving more than 200 patients, serum gastrin levels increased during the first 1 to 2 weeks of once‑daily administration of therapeutic doses of omeprazole in parallel with inhibition of acid secretion. No further increase in serum gastrin occurred with continued treatment. Gastrin values returned to pretreatment levels, usually within 1 to 2 weeks after discontinuation of therapy.

Increased gastrin causes enterochromaffin-like cell hyperplasia and increased serum Chromogranin A (CgA) levels. The increased CgA levels may cause false positive results in diagnostic investigations for neuroendocrine tumors [see Warnings and Precautions (5.12)] .

Other Effects

Systemic effects of omeprazole in the Central Nervous System (CNS), cardiovascular, and respiratory systems have not been found to date. Omeprazole, given in oral doses of 30 or 40 mg for 2 to 4 weeks, had no effect on thyroid function, carbohydrate metabolism, or circulating levels of parathyroid hormone, cortisol, estradiol, testosterone, prolactin, cholecystokinin or secretin.

No effect on gastric emptying of the solid and liquid components of a test meal was demonstrated after a single dose of omeprazole 90 mg. In healthy subjects, a single intravenous dose of omeprazole (0.35 mg/kg) had no effect on intrinsic factor secretion. No systematic dose-dependent effect has been observed on basal or stimulated pepsin output in humans. However, when intragastric pH is maintained at 4.0 or above, basal pepsin output is low, and pepsin activity is decreased.

As do other agents that elevate intragastric pH, omeprazole administered for 14 days in healthy subjects produced a significant increase in the intragastric concentrations of viable bacteria. The pattern of the bacterial species was unchanged from that commonly found in saliva. All changes resolved within three days of stopping treatment.

The course of Barrett’s esophagus in 106 patients was evaluated in a U.S. double-blind controlled study of omeprazole 40 mg twice daily for 12 months followed by 20 mg twice daily for 12 months or ranitidine 300 mg twice daily for 24 months. No clinically significant impact on Barrett’s mucosa by antisecretory therapy was observed. Although neosquamous epithelium developed during antisecretory therapy, complete elimination of Barrett’s mucosa was not achieved. No significant difference was observed between treatment groups in development of dysplasia in Barrett’s mucosa, and no patient developed esophageal carcinoma during treatment. No significant differences between treatment groups were observed in development of ECL cell hyperplasia, corpus atrophic gastritis, corpus intestinal metaplasia, or colon polyps exceeding 3 mm in diameter.

12.3 Pharmacokinetics

Absorption

The bioavailability and pharmacokinetics of KONVOMEP was assessed in 57 healthy male and female volunteers following a 40 mg dose under fasted conditions. The absorption of omeprazole was rapid with a median time to peak plasma concentration of 0.33 hour (range 0.17 to 1.3 hr.). The mean peak plasma concentration (SD) was 1250 ng/mL (470) and the AUC(0-inf)(SD) was 1640 h*ng/mL (1050).

Omeprazole is a time-dependent autoinhibitor of CYP2C19. The bioavailability of omeprazole from omeprazole and sodium bicarbonate for oral suspension increases upon repeated administration.

Following repeated once-daily dosing of omeprazole at a dose of 40 mg with sodium bicarbonate, a higher omeprazole mean Cmax(1.4-fold on Day 7) and increased AUC (2-fold on Day 7) were observed. The increase in mean steady-state AUC (on Day 7) for omeprazole at a dose of 40 mg was greater than dose proportional relative to a lower dose.

When omeprazole and sodium bicarbonate for oral suspension 40 mg was administered in a two-dose loading regimen, the omeprazole AUC0-inf(ng•hr/mL) was 1665 after Dose 1 and 3356 after Dose 2, while Tmaxwas approximately 30 minutes for both Dose 1 and Dose 2.

When omeprazole and sodium bicarbonate for oral suspension 40 mg is administered one hour after a meal, the omeprazole AUC is reduced by approximately 27% and 22%, respectively, relative to administration one hour prior to a meal [see Dosage and Administration (2.3)] .

Distribution

Omeprazole is bound to plasma proteins. Protein binding is approximately 95%.

Elimination

Metabolism

Omeprazole is extensively metabolized by the cytochrome P450 (CYP) enzyme system. The major part of its metabolism is dependent on the polymorphically expressed CYP2C19 [see Clinical Pharmacology (12.5)] , responsible for the formation of hydroxyomeprazole, the major metabolite in plasma. The remaining part is dependent on another specific isoform, CYP3A4, responsible for the formation of omeprazole sulphone.

The mean plasma omeprazole half-life following administration of omeprazole/sodium bicarbonate oral suspension in healthy subjects is approximately 1 hour (range 0.4 to 4.2 hours), and the total body clearance is 500 to 600 mL/min.

Excretion

Following single-dose oral administration of a buffered solution of omeprazole, the majority of the dose (about 77%) is eliminated in urine as at least six metabolites. Two metabolites have been identified as hydroxyomeprazole and the corresponding carboxylic acid. The remainder of the dose was recoverable in feces. This implies a significant biliary excretion of the metabolites of omeprazole. Three metabolites have been identified in plasma – the sulfide and sulfone derivatives of omeprazole, and hydroxyomeprazole. These metabolites have very little or no antisecretory activity.

Special Populations

Geriatric Patients

The elimination rate of omeprazole was somewhat decreased in the elderly, and bioavailability was increased. Omeprazole was 76% bioavailable when a single 40 mg oral dose of omeprazole (buffered solution) was administered to healthy elderly subjects versus 58% in young subjects given the same dose. Nearly 70% of the dose was recovered in urine as metabolites of omeprazole, and no unchanged drug was detected. The plasma clearance of omeprazole was 250 mL/min (about half that of young subjects), and its plasma half-life averaged one hour, similar to that of young healthy subjects.

Male and Female Patients

There are no known differences in the absorption or excretion of omeprazole between males and females.

Racial or Ethnic Groups

[see Clinical Pharmacology (12.5)] .

Patients with Renal Impairment

In patients with chronic renal impairment (creatinine clearance ranged between 10 and 62 mL/min/1.73 m^2), the disposition of omeprazole was very similar to that in healthy subjects, although there was a slight increase in bioavailability. Because urinary excretion is a primary route of excretion of omeprazole metabolites, their elimination slowed in proportion to the decreased creatinine clearance. This increase in bioavailability is not considered to be clinically meaningful.

Patients with Hepatic Impairment

In patients with chronic hepatic disease classified as Child-Pugh Class A (n=3), B (n=4) and C (n=1), the bioavailability of omeprazole increased to approximately 100% compared to healthy subjects, reflecting decreased first-pass effect, and the plasma half-life of the drug increased to nearly 3 hours compared to the mean half-life of 0.5 to 1 hour in healthy subjects. Plasma clearance averaged 70 mL/min, compared to a value of 500 to 600 mL/min in healthy subjects.

Drug Interactions Studies

Effect of Omeprazole on Other Drugs

Omeprazole is a time-dependent inhibitor of CYP2C19 and can increase the systemic exposure of co‑administered drugs that are CYP2C19 substrates. In addition, administration of omeprazole increases intragastric pH and can alter the systemic exposure of certain drugs that exhibit pH-dependent solubility [see Drug Interactions (7)] .

Antiretrovirals

For some antiretroviral drugs, such as rilpivirine, atazanavir and nelfinavir, decreased serum concentrations have been reported when given together with omeprazole [see Drug Interactions (7)] .

Rilpivirine:Following multiple doses of rilpivirine (150 mg, daily) and omeprazole (20 mg, daily), AUC was decreased by 40%, Cmaxby 40%, and Cminby 33% for rilpivirine.

Nelfinavir:Following multiple doses of nelfinavir (1250 mg, twice daily) and omeprazole (40 mg daily), AUC was decreased by 36% and 92%, Cmaxby 37% and 89% and Cminby 39% and 75% respectively for nelfinavir and M8.

Atazanavir:Following multiple doses of atazanavir (400 mg, daily) and omeprazole (40 mg, daily, 2 hours before atazanavir), AUC was decreased by 94%, Cmaxby 96%, and Cminby 95%.

Saquinavir:Following multiple dosing of saquinavir/ritonavir (1000/100 mg) twice daily for 15 days with omeprazole 40 mg daily co-administered days 11 to 15. AUC was increased by 82%, Cmaxby 75%, and Cminby 106%. The mechanism behind this interaction is not fully elucidated. Therefore, clinical and laboratory monitoring for saquinavir toxicity is recommended during concurrent use with omeprazole.

Clopidogrel

In a crossover clinical study, 72 healthy subjects were administered clopidogrel (300 mg loading dose followed by 75 mg per day) alone and with omeprazole (80 mg at the same time as clopidogrel) for 5 days. The exposure to the active metabolite of clopidogrel was decreased by 46% (Day 1) and 42% (Day 5) when clopidogrel and omeprazole were administered together.

Results from another crossover study in healthy subjects showed a similar pharmacokinetic interaction between clopidogrel (300 mg loading dose/75 mg daily maintenance dose) and omeprazole 80 mg daily when coadministered for 30 days. Exposure to the active metabolite of clopidogrel was reduced by 41% to 46% over this time period.

In another study, 72 healthy subjects were given the same doses of clopidogrel and 80 mg omeprazole, but the drugs were administered 12 hours apart; the results were similar, indicating that administering clopidogrel and omeprazole at different times does not prevent their interaction [see Warnings and Precautions (5.8), Drug Interactions (7)] .

Mycophenolate Mofetil

Administration of omeprazole 20 mg twice daily for 4 days and a single 1000 mg dose of MMF approximately one hour after the last dose of omeprazole to 12 healthy subjects in a crossover study resulted in a 52% reduction in the Cmaxand 23% reduction in the AUC of MPA [see Drug Interactions (7)] .

Cilostazol

Omeprazole acts as an inhibitor of CYP2C19. Omeprazole, given in doses of 40 mg daily for one week to 20 healthy subjects in cross-over study, increased Cmaxand AUC of cilostazol by 18% and 26% respectively. The Cmaxand AUC of one of the active metabolites, 3,4-dihydro-cilostazol, which has 4 to 7 times the activity of cilostazol, were increased by 29% and 69%, respectively. Co-administration of cilostazol with omeprazole is expected to increase concentrations of cilostazol and the above‑mentioned active metabolite [see Drug Interactions (7)] .

Diazepam

Concomitant administration of omeprazole 20 mg once daily and diazepam 0.1 mg/kg given intravenously resulted in 27% decrease in clearance and 36% increase in diazepam half-life [see Drug Interactions (7)] .

Digoxin

Concomitant administration of omeprazole 20 mg once daily and digoxin in healthy subjects increased the bioavailability of digoxin by 10% (30% in two subjects) [see Drug Interactions (7)] .

Effect of Other Drugs on Omeprazole

Voriconazole

Concomitant administration of omeprazole and voriconazole (a combined inhibitor of CYP2C19 and CYP3A4) resulted in more than doubling of the omeprazole exposure. When voriconazole (400 mg every 12 hours for one day, followed by 200 mg once daily for 6 days) was given with omeprazole (40 mg once daily for 7 days) to healthy subjects, the steady-state Cmaxand AUC0-24of omeprazole significantly increased: an average of 2 times (90% CI: 1.8, 2.6) and 4 times (90% CI: 3.3, 4.4), respectively, as compared to when omeprazole was given without voriconazole [see Drug Interactions (7)] .

12.5 Pharmacogenomics

CYP2C19, a polymorphic enzyme, is involved in the metabolism of omeprazole. The CYP2C19*1 allele is fully functional while the CYP2C19*2 and *3 alleles are nonfunctional. There are other alleles associated with no or reduced enzymatic function. Patients carrying two fully functional alleles are extensive metabolizers and those carrying two loss-of-function alleles are poor metabolizers. In extensive metabolizers, omeprazole is primarily metabolized by CYP2C19. The systemic exposure to omeprazole varies with a patient’s metabolism status: poor metabolizers > intermediate metabolizers > extensive metabolizers. Approximately 3% of Caucasians and 15 to 20% of Asians are CYP2C19 poor metabolizers.

In pharmacokinetic studies of single 20 mg omeprazole dose, the AUC of omeprazole in Asian subjects was approximately four-fold of that in Caucasians.

13 NONCLINICAL TOXICOLOGY

13.1 Carcinogenesis, Mutagenesis, Impairment of Fertility

In two 24-month carcinogenicity studies in rats, omeprazole at daily doses of 1.7, 3.4, 13.8, 44.0 and 140.8 mg/kg/day (approximately 0.4 to 34.2 times the human dose of 40 mg/day on a body surface area basis) produced gastric ECL cell carcinoids in a dose-related manner in both male and female rats; the incidence of this effect was markedly higher in female rats, which had higher blood levels of omeprazole. Gastric carcinoids seldom occur in the untreated rat. In addition, ECL cell hyperplasia was present in all treated groups of both sexes. In one of these studies, female rats were treated with 13.8 mg omeprazole/kg/day (approximately 3.36 times the human dose of 40 mg/day on a body surface area basis) for one year, then followed for an additional year without the drug. No carcinoids were seen in these rats. An increased incidence of treatment‑related ECL cell hyperplasia was observed at the end of one year (94% treated versus 10% controls). By the second year the difference between treated and control rats was much smaller (46% versus 26%) but still showed more hyperplasia in the treated group. Gastric adenocarcinoma was seen in one rat (2%). No similar tumor was seen in male or female rats treated for two years. For this strain of rat, no similar tumor has been noted historically, but a finding involving only one tumor is difficult to interpret. In a 52-week toxicity study in Sprague Dawley rats, brain astrocytomas were found in a small number of males that received omeprazole at dose levels of 0.4, 2 and 16 mg/kg/day (about 0.1 to 3.9 times the human dose of 40 mg/day on a body surface area basis). No astrocytomas were observed in female rats in this study. In a 2-year carcinogenicity study in Sprague Dawley rats, no astrocytomas were found in males and females at the high dose of 140.8 mg/kg/day (about 34 times the human dose of 40 mg/day on a body surface area basis). A 78-week mouse carcinogenicity study of omeprazole did not show increased tumor occurrence, but the study was not conclusive. A 26-week p53 (+/-) transgenic mouse carcinogenicity study was not positive.

Omeprazole was positive for clastogenic effects in an in vitrohuman lymphocyte chromosomal aberration assay, in one of two in vivomouse micronucleus tests, and in an in vivobone marrow cell chromosomal aberration assay. Omeprazole was negative in the in vitroAmes test, an in vitromouse lymphoma cell forward mutation assay and an in vivorat liver DNA damage assay.

In a 24-month carcinogenicity studies in rats, a dose-related significant increase in gastric carcinoid tumors and ECL cell hyperplasia was observed in both male and female animals. Carcinoid tumors have also been observed in rats subjected to fundectomy or long-term treatment with other proton pump inhibitors or high doses of H2-receptor antagonists.

Omeprazole at oral doses up to 138 mg/kg/day (about 33.6 times the human dose of 40 mg/day on a body surface area basis) was found to have no effect on the fertility and general reproductive performance in rats.

14 CLINICAL STUDIES

14.1 Active Benign Gastric Ulcer

The effectiveness of KONVOMEP has been established, in part, based on studies of an oral delayed-release omeprazole product for the treatment of active benign gastric ulcer.

In a U.S. multicenter, double-blind study of two doses of omeprazole and placebo in 520 patients with endoscopically diagnosed gastric ulcer, the following results were obtained with 40 mg omeprazole and placebo. (see Table 8.)

Table 8: Treatment of Gastric Ulcer % of Patients Healed
 | % of Patients Healed
 | Omeprazole 40 mg once daily (n = 214) | Placebo (n = 104)
Week 4 | 55.6 [p < 0.01 omeprazole 40 mg versus placebo] | 30.8
Week 8 | 82.7 | 48.1

For the stratified groups of patients with ulcer size less than or equal to 1 cm, no difference in healing rates between 40 mg and the lower omeprazole dosage was detected at either 4 or 8 weeks. For patients with ulcer size greater than 1 cm, 40 mg omeprazole was significantly more effective than the lower omeprazole dosage at 8 weeks.

In a foreign, multinational, double-blind study of 602 patients with endoscopically diagnosed gastric ulcer, two doses of omeprazole and ranitidine 150 mg twice a day were evaluated. The following results were obtained with 40 mg omeprazole and ranitidine (see Table 9).

Table 9: Treatment of Gastric Ulcer % of Patients Healed
 | % of Patients Healed
 | Omeprazole 40 mg once daily (n = 187) | Ranitidine 150 mg twice daily (n = 199)
Week 4 | 78.1 [p < 0.01 omeprazole 40 mg versus ranitidine] | 56.3
Week 8 | 91.4 | 78.4

14.2 Reduction of Risk of Upper Gastrointestinal Bleeding in Critically Ill Patients

The effectiveness of KONVOMEP has been established, in part, based on studies of another omeprazole and sodium bicarbonate oral suspension product for the reduction of risk of upper GI bleeding in critically ill adult patients.

A double-blind, multicenter, randomized, non-inferiority clinical trial was conducted to compare omeprazole and sodium bicarbonate oral suspension 40 mg/1680 mg and intravenous cimetidine for the reduction of risk of upper gastrointestinal (GI) bleeding in critically ill patients (mean APACHE II score = 23.7). The primary endpoint was significant upper GI bleeding defined as bright red blood which did not clear after adjustment of the nasogastric tube and a 5 to 10 minutes lavage, or persistent Gastroccult positive coffee grounds for 8 consecutive hours which did not clear with 100 mL lavage. Omeprazole and sodium bicarbonate oral suspension was administered as two doses of 40 mg omeprazole and 1680 mg sodium bicarbonate 6 to 8 hours apart on the first day via orogastric or nasogastric tube, followed by 40 mg omeprazole and 1680 mg sodium bicarbonate once daily thereafter. Cimetidine was administered intravenously as a 300 mg bolus, followed by 50 to 100 mg/hour continuously thereafter. Treatment was administered for up to 14 days (mean = 6.8 days). A total of 359 patients were studied, age range 16 to 91 years (mean age of 56 years), 58.5% were males, and 64% were Caucasians. The results of the study showed that omeprazole and sodium bicarbonate oral suspension was non-inferior to intravenous cimetidine, 7/178 (3.9%) patients in the omeprazole and sodium bicarbonate oral suspension group vs. 10/181 (5.5%) patients in the cimetidine group experienced clinically significant upper GI bleeding.

16 HOW SUPPLIED/STORAGE AND HANDLING

How Supplied

KONVOMEP (omeprazole and sodium bicarbonate for oral suspension) 2 mg/84 mg per mL is supplied as:

A kit containing two bottles:

- one bottle with child resistant closure of omeprazole USP, a white to off-white powder and
- one bottle of pre‑measured strawberry‑flavored slightly hazy red diluent containing sodium bicarbonate (see table below).

Prior to dispensing, reconstitute KONVOMEP for oral suspension [see Dosage and Administration (2.3)] .

Final Volume of KONVOMEP after reconstitution | Kit Contents | NDC Numbers
90 mL | Bottle of 0.18 g omeprazole powder | 65628-270-03
90 mL | Bottle of diluent containing sodium bicarbonate 7.56 g per 90 mL | 65628-271-03
90 mL | Konvomep Kit | 65628-272-03
150 mL | Bottle of 0.3 g omeprazole powder | 65628-270-05
150 mL | Bottle of diluent containing sodium bicarbonate 12.6 g per 150 mL | 65628-271-05
150 mL | Konvomep Kit | 65628-272-05
300 mL | Bottle of 0.6 g omeprazole powder | 65628-270-10
300 mL | Bottle of diluent containing sodium bicarbonate 25.2 g per 300 mL | 65628-271-10
300 mL | Konvomep Kit | 65628-272-10

Storage

- Store KONVOMEP kit in the refrigerator, 2°C to 8°C (36°F to 46°F).
- Store reconstituted suspension of KONVOMEP in the refrigerator, 2°C to 8°C (36°F to 46°F); discard unused reconstituted suspension after 30 days.
- Keep containers tightly closed.
- Protect containers from light.
- Protect containers from freezing.

17 PATIENT COUNSELING INFORMATION

Advise the patient to read the FDA-approved patient labeling (Medication Guide).

Acute Tubulointerstitial Nephritis

Advise the patient to call their healthcare provider immediately if they experience signs and/or symptoms associated with acute tubulointerstitial nephritis [see Warnings and Precautions (5.2)] .

Sodium Bicarbonate Buffer Content

Inform patients on a sodium-restricted diet or patients at risk of developing congestive heart failure of the sodium content of KONVOMEP (526 mg or 22.8 mEq total sodium per 40 mg dose).

Advise patients that:

- chronic use of bicarbonate with calcium or milk can cause milk-alkali syndrome
- chronic use of sodium bicarbonate may cause systemic alkalosis
- increased sodium intake can cause swelling and weight gain

If any of these occur, instruct patients to contact their healthcare provider [see Warnings and Precautions (5.3)] .

Clostridium difficile-Associated Diarrhea

Advise the patient to immediately call their healthcare provider if they experience diarrhea that does not improve [see Warnings and Precautions (5.4)] .

Bone Fracture

Advise the patient to report any fractures, especially of the hip, wrist, or spine, to their healthcare provider [see Warnings and Precautions (5.5)] .

Severe Cutaneous Adverse Reactions

Advise the patient to immediately call their healthcare provider for any new or worsening of symptoms associated with cutaneous or systemic lupus erythematosus [see Warnings and Precautions (5.6)] .

Cutaneous and Systemic Lupus Erythematosus

Advise the patient to immediately call their healthcare provider for any new or worsening of symptoms associated with cutaneous or systemic lupus erythematosus [see Warnings and Precautions (5.7)] .

Cyanocobalamin (Vitamin B-12) Deficiency

Advise the patient to report any clinical symptoms that may be associated with cyanocobalamin deficiency to their healthcare provider if they have been receiving KONVOMEP for longer than 3 years [see Warnings and Precautions (5.9)] .

Hypomagnesemia and Mineral Metabolism

Advise the patient to report any clinical symptoms that may be associated with hypomagnesemia, hypocalcemia, and/or hypokalemia to their healthcare provider, if they have been receiving KONVOMEP for at least 3 months [see Warnings and Precautions (5.10)] .

Drug Interactions

Advise patients to report to their healthcare provider if they start treatment with rilpivirine-containing products, clopidogrel, St. John’s wort or rifampin, or if they take high-dose methotrexate [see Contraindications (4) and Warnings and Precautions (5.8, 5.11and 5.13)] .

Administration

- Instruct the patient or caregiver to shake the reconstituted suspension well before each use.
- Advise patients that KONVOMEP may be administered orally, or via a nasogastric or orogastric tube.
- Instruct patients or caregivers to suspend enteral feeding approximately 3 hours before and 1 hour after administration of KONVOMEP by nasogastric or orogastric tube [see Dosage and Administration (2.3)] .

Store reconstituted KONVOMEP suspension in the refrigerator. Discard the reconstituted KONVOMEP suspension after 30 days.

KONVOMEP is a registered trademark of Azurity Pharmaceuticals, Inc.

Manufactured for:
Azurity Pharmaceuticals, Inc.
Woburn, MA 01801 USA

Patent: https://azurity.com/patents

This product’s labeling may have been updated. For current Full Prescribing Information, please visit www.konvomep.com

PN: 65628-0288

Rev: 04 04/2024

Medication Guide

KONVOMEP®(Kan-vo-mep)
(omeprazole and sodium bicarbonate for oral suspension)

What is the most important information I should know about KONVOMEP?

KONVOMEP may help your acid-related symptoms, but you could still have serious stomach problems. Talk with your doctor.

KONVOMEP can cause serious side effects, including:

- A type of kidney problem (acute tubulointerstitial nephritis).Some people who take proton pump inhibitor (PPI) medicines, including KONVOMEP, may develop a kidney problem called acute tubulointerstitial nephritis that can happen at any time during treatment with KONVOMEP. Call your doctor right away if you have a decrease in the amount that you urinate or if you have blood in your urine.
- KONVOMEP contains sodium bicarbonate.Long-term use of bicarbonate with calcium or milk can cause a condition called “milk-alkali syndrome”. Long-term use of sodium bicarbonate can cause a condition called “systemic alkalosis”. Talk to your doctor about any questions you may have. Too much sodium can cause swelling and weight gain. Tell your doctor if you are on a low‑sodium diet or if you have Bartter’s Syndrome (a rare kidney disorder). Tell your doctor right away if you have confusion, shaking hands, dizziness, muscle twitching, nausea, vomiting, and numbness or tingling in the face, arms, or legs.
- Diarrhea caused by an infection (Clostridium difficile) in your intestines. Call your doctor right away if you have watery stools or stomach pain that does not go away. You may or may not have a fever.
- Bone fractures (hip, wrist, or spine).Bone fractures in the hip, wrist or spine may happen in people who take multiple daily doses of PPI medicines and for a long period of time (a year or longer). Tell your doctor if you have bone fracture, especially in the hip, wrist, or spine.
- Certain types of lupus erythematosus.Lupus erythematosus is an autoimmune disorder (the body’s immune cells attack other cells or organs in the body). Some people who take PPI medicines, including KONVOMEP, may develop certain types of lupus erythematosus or have worsening of the lupus they already have. Call your doctor right away if you have new or worsening joint pain or a rash on your cheeks or arms that gets worse in the sun.

Talk to your doctor about your risk of these serious side effects.

KONVOMEP can have other serious side effects. See “What are the possible side effects of KONVOMEP?”

What is KONVOMEP?

KONVOMEP is a combination of omeprazole, a proton pump inhibitor (PPI) and sodium bicarbonate.

KONVOMEPis used:

- in adults for up to 8 weeks for the healing of stomach ulcers.
- in critically ill adults to lower the risk of stomach bleeding.

It is not known if KONVOMEP is safe and effective in children.

Do not take KONVOMEP if you are:

- allergic to omeprazole, any other PPI medicine, or any of the ingredients in KONVOMEP. See the end of this Medication Guide for a complete list of ingredients in KONVOMEP.
- taking a medicine that contains rilpivirine, used to treat HIV-1 (Human Immunodeficiency Virus).

Before taking KONVOMEP, tell your doctor about all of your medical conditions, including if you:

- have low magnesium, calcium, or potassium levels in your blood.
- have problems with the acid-base (pH) balance in your body.
- have heart failure.
- are on a low-sodium diet.
- have Bartter’s syndrome (a rare kidney problem).
- are pregnant or plan to become pregnant. It is not known if KONVOMEP will harm your unborn baby.
- are breastfeeding or plan to breastfeed. KONVOMEP can pass into your breast milk. Talk with your doctor about the best way to feed your baby if you take KONVOMEP.

Tell your doctor about all the medicines you take,including prescription and over‑the counter medications, vitamins and herbal supplements.

Especially tell your doctor if you take:

- digoxin
- clopidogrel
- St. John’s wort (Hypericum perforatum)
- rifampin
- methotrexate

Ask your doctor or pharmacist for a list of these medicines, if you are not sure.

Know the medicines that you take. Keep a list of them to show your doctor and pharmacist when you get a new medicine.

How should I take KONVOMEP?

- Take KONVOMEP exactly as prescribed by your doctor.
- KONVOMEP is mixed (reconstituted) by a healthcare provider, and you will receive KONVOMEP as an oral suspension that can be taken by mouth or given through a nasogastric or orogastric tube.
- Shake the KONVOMEP oral suspension well before each use.
- Measure the KONVOMEP oral suspension with an accurate measuring device. Ask your pharmacist to recommend a measuring device and for instructions on how to measure the correct dose.
- If KONVOMEP is given through a nasogastric or orogastric tube, it is important to stop enteral feeding at least 3 hours beforegiving KONVOMEP. You can start enteral feeding again at least 1 hour aftergiving KONVOMEP.
- Do not change your dose or stop taking KONVOMEP without talking to your doctor.
- If you miss a dose of KONVOMEP, take it as soon as you remember. If it is almost time for your next dose, do not take the missed dose. Take the next dose at your regular time. Do not take two doses to make up for a missed dose.
- If you take too much KONVOMEP, call your doctor or Poison Control Center at 1-800-222-1222 right away, or go to the nearest hospital emergency room.

What are the possible side effects of KONVOMEP?

KONVOMEP may cause serious side effects, including:

- See “What is the most important information I should know about KONVOMEP?”
- Low vitamin B-12 levelsin your body can happen in people who have taken KONVOMEP for a long time (more than 3 years). Tell your doctor if you have symptoms of low vitamin B-12 levels, including shortness of breath, lightheadedness, irregular heartbeat, muscle weakness, pale skin, feeling tired, mood changes, and tingling or numbness in the arms and legs.
- Low magnesium levels in your body can happen in people who have taken KONVOMEPfor at least 3 months. Tell your doctor right away if you have symptoms of low magnesium levels, including seizures, dizziness, irregular heartbeat, jitteriness, muscle aches or weakness, and spasms of hands, feet, or voice.
- Stomach growths (fundic gland polyps).People who take PPI medicines for a long time have an increased risk of developing a certain type of stomach growths called fundic gland polyps, especially after taking PPI medicines for more than 1 year.
- Severe skin reactions.KONVOMEP can cause rare but severe skin reactions that may affect any part of your body. These serious skin reactions may need to be treated in a hospital and may be life threatening:
  - Skin rash which may have blistering, peeling or bleeding on any part of your skin (including your lips, eyes, mouth, nose, genitals, hands or feet).
  - You may also have fever, chills, body aches, shortness of breath, or enlarged lymph nodes.

Stop taking KONVOMEP and call your doctor right away. These symptoms may be the first sign of a severe skin reaction.

The most common side effects of KONVOMEP include:

- headache
- abdominal pain
- nausea

- diarrhea
- vomiting
- gas

These are not all the possible side effects of KONVOMEP. Call your doctor for medical advice about side effects. You may report side effect to FDA at 1‑800‑FDA‑1088.

You may also report side effects to Azurity Pharmaceuticals, Inc. at 1‑800-461‑7449.

How should I store KONVOMEP?

- Store KONVOMEP oral suspension in the refrigerator between 36°F to 46°F (2°C to 8°C).
- Keep the KONVOMEP container tightly closed. Protect the container from light.
- Do not freeze KONVOMEP.
- Throw away (discard) any unused KONVOMEP oral suspension after 30 days.

Keep KONVOMEP and all medicines out of the reach of children.

General information about the safe and effective use of KONVOMEP.

Medicines are sometimes prescribed for purposes other than those listed in a Medication Guide. Do not use KONVOMEP for any condition for which it was not prescribed. Do not give KONVOMEP to other people, even if they have the same symptoms that you have. It may harm them.

You can also ask your doctor or pharmacist for information about KONVOMEP that is written for health professionals.

What are the ingredients in KONVOMEP?

Active ingredients: omeprazole and sodium bicarbonate

Inactive ingredients in KONVOMEP:benzyl alcohol, carboxymethylcellulose sodium, FD&C Red No. 40, poloxamer 188, purified water, simethicone emulsion, sodium citrate (dihydrate), sorbitol solution, strawberry flavor (natural and artificial flavors, propylene glycol and glycerin) and sucralose.

Manufactured for:
Azurity Pharmaceuticals, Inc.
Woburn, MA 01801 USA

For more information, go to www.azurity.com or call 1-800-461-7449.

This Medication Guide has been approved by the U.S. Food and Drug Administration

Issued: 08/2023
PN: MC-00691
REV: 01 08/2023

PRINCIPAL DISPLAY PANEL – Carton Label

NDC 65628-272-10

Rx Only

KONVOMEP®
(omeprazole and sodium bicarbonate
for oral suspension)

2 mg/84 mg per mL*

*300 mL final volume. When reconstituted, each mL contains
2 mg omeprazole, USP, and 84 mg sodium bicarbonate, USP.

EACH KIT INCLUDES:

- One bottle containing 0.6 g omeprazole powder
- One bottle containing 25.2 g sodium bicarbonate
  in 300 mL strawberry-flavored Diluent
- One Full Prescribing Information
- One Medication Guide

Shake well before each use

IMPORTANT NOTE TO PHARMACIST:
Must Reconstitute before dispensing

azurity®
pharmaceuticls

Dispense Medication Guide to each patient.

300 mL final volume after reconstitution

PRINCIPAL DISPLAY PANEL – Drug Product Label

NDC 65628-270-10

Rx Only

KONVOMEP®
(omeprazole and sodium bicarbonate
for oral suspension)

2 mg/84 mg per mL*

* 300 mL final volume. When reconstituted,
each mL contains 2 mg omeprazole, USP,
and 84 mg sodium bicarbonate, USP.

DISPENSE THIS BOTTLE TO THE PATIENT

IMPORTANT NOTE TO PHARMACIST: Must
Reconstitute before dispensing. This bottle
contains 0.6 g of omeprazole powder. Add
diluent provided.

Shake well before each use.

Must be used within 30 daysafter reconstitution.
Store Refrigerated, 2°C to 8°C (36°F to 46°F)

Recommended Dosage: See Prescribing Information

Dispense Medication Guide to each patient.

Manufactured by:
azurity®
pharmaceuticals
Woborn, MA 01801 USA

Discard after:
____/____/____

R02
08/23

PRINCIPAL DISPLAY PANEL – Diluent Label

NDC 65628-271-10

Rx Only

DILUENT
for RECONSTITUTIONof
Konvomep®(omeprazole
and sodium bicarbonate
for oral suspension)

Contains:sodium bicarbonate, USP, 84 mg/mL

IMPORTANT NOTE TO PHARMACIST:
Add the contents of this bottle to the bottle
containing omeprazole powder according
to the preparation instructions in the Full
Prescribing Information.

Store Refrigerated, 2°C to 8°C (36°F to 46°F)

Recommended Dosage:
See Prescribing Information

Net Contents 25.2 g sodium bicarbonate in 300 mL.

Manufactured for:
azurity®
pharmaceuticals
Woborn, MA 01801 USA

Strawberry
Flavor

R02
08/23